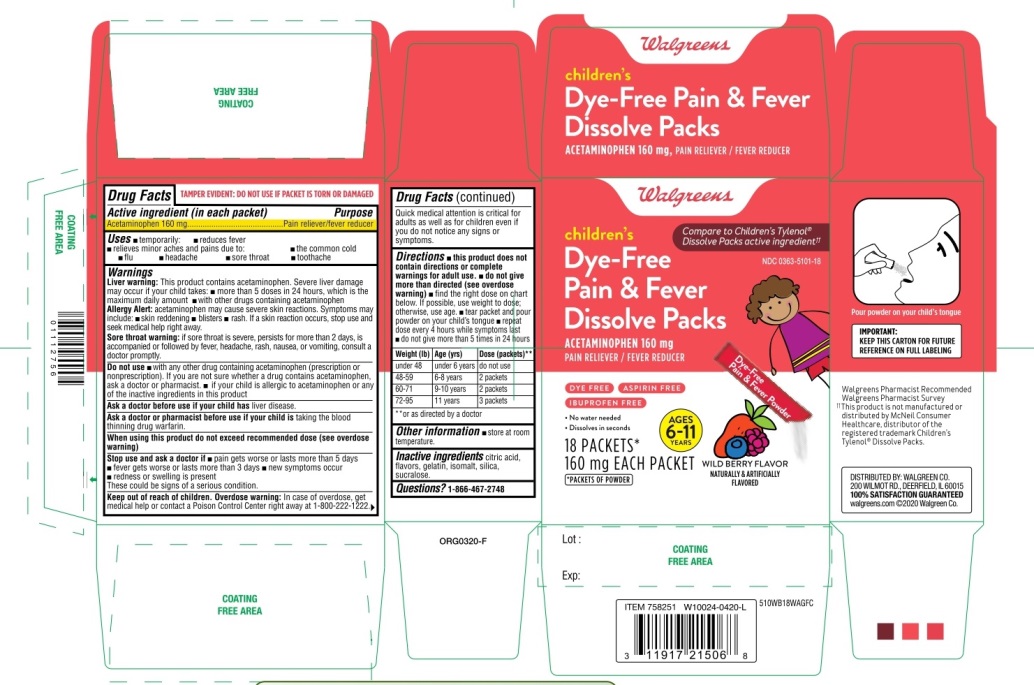 DRUG LABEL: Childrens Pain and Fever

NDC: 0363-5101 | Form: POWDER
Manufacturer: WALGREENS CO.
Category: otc | Type: HUMAN OTC DRUG LABEL
Date: 20251125

ACTIVE INGREDIENTS: ACETAMINOPHEN 160 mg/1 1
INACTIVE INGREDIENTS: CITRIC ACID MONOHYDRATE; GELATIN, UNSPECIFIED; ISOMALT; SILICON DIOXIDE; SUCRALOSE

Walgreens Children's Dye-Free Pain & Fever Dissolve Packs Acetaminophen

Drug Facts

Active ingredient (in each packet)

Acetaminophen 160 mg

Purpose

Pain reliever/fever reducer

Uses

- temporarily:
- reduces fever
- relieves minor aches and pains due to:
- the common cold
- flu
- headache
- sore throat
- toothache

Warnings

Liver warning

This product contains acetaminophen. Severe liver damage may occur if your child takes

- more than 5 doses in 24 hours, which is the maximum daily amount
- with other drugs containing acetaminophen

Allergy alert:acetaminophen may cause severe skin reactions. Symptoms may include:

- skin reddening
- blisters
- rash

If a skin reaction occurs, stop use and seek medical help right away.

Sore throat warning:if sore throat is severe, persists for more than 2 days, is accompanied or followed by fever, headache, rash, nausea, or vomiting, consult a doctor promptly.

Do not use

- with any other drug containing acetaminophen (prescription or nonprescription). If you are not sure whether a drug contains acetaminophen, ask a doctor or pharmacist.
- if your child is allergic to acetaminophen or any of the inactive ingredients in this product

Ask a doctor before use if your child hasliver disease

Ask a doctor or pharmacist before use if your child istaking the blood thinning drug warfarin

When using this product do not exceed recommended dose (see overdose warning)

Stop use and ask a doctor if

- pain gets worse or lasts more than 5 days
- fever gets worse or lasts more than 3 days
- new symptoms occur
- redness or swelling is present

These could be signs of a serious condition.

Keep out of reach of children.

Overdose warning

In case of overdose, get medical help or contact a Poison Control Center right away. (1-800-222-1222).

Quick medical attention is critical for adults as well as for children even if you do not notice any signs or symptoms.

Directions

- this product does not contain directions or complete warnings for adult use.
- do not give more than directed (see overdose warning)
- find right dose on chart. If possible, use weight to dose; otherwise, use age.
- tear packet and pour powder on your child's tongue
- repeat dose every 4 hours while symptoms last
- do not give more than 5 times in 24 hours

Weight (lb) | Age (yrs.) | Dose (packets)**
under 48 | under 6 years | do not use
48-59 | 6-8 years | 2 packets
60-71 | 9-10 years | 2 packets
72-95 | 11 years | 1. packets

Other information

- store at room temperature

TAMPER EVIDENT: DO NOT USE IF PACKET IS TORN OR DAMAGED

Inactive ingredients

citric acid, flavor, gelatin, isomalt, silica, sucralose

Questions?

1-866-467-2748

PRINCIPAL DISPLAY PANEL

NDC 0363-5101-18

Children's

Dye-Free

Pain & Fever Dissolve Packs

ACETAMINOPHEN 160 mg
PAIN RELIEVER/FEVER REDUCER

DYE FREE, ASPIRIN FREE, IBUPROFEN FREE

- No water needed
- Dissolves in seconds

AGES 6-11 YEARS

18 PACKETS*
160 mg EACH PACKET

WILD BERRY FLAVOR

NATURALLY AND ARTIFICIALLY FLAVORED

*PACKETS OF POWDER

Pour powder on your child’s tongue

IMPORTANT:Keep this carton for future reference on full labeling.

Walgreens Pharmacist Recommended

Walgreens Pharmacist Survey

††This product is not manufactured or distributed by McNeil Consumer Healthcare, distributor of the registered trademark Children’s Tylenol® Dissolve Packs.

Distributed by:

WALGREEN CO.

200 WILMOT RD., CEERFIELD, IL 60015

100% SATISFACTION GUARANTEED

walgreens.com © 2020 Walgreen Co.